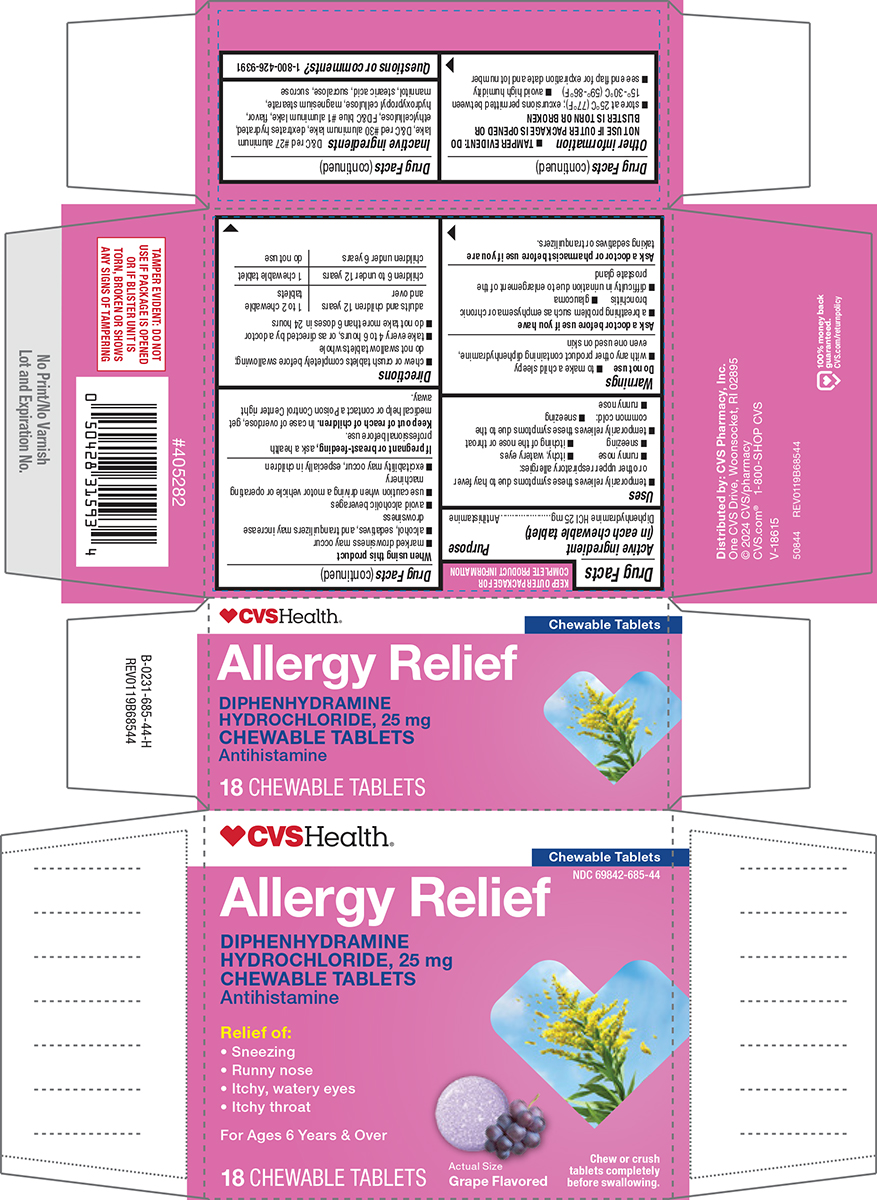 DRUG LABEL: Allergy Relief
NDC: 69842-685 | Form: TABLET, CHEWABLE
Manufacturer: CVS PHARMACY
Category: otc | Type: HUMAN OTC DRUG LABEL
Date: 20250510

ACTIVE INGREDIENTS: DIPHENHYDRAMINE HYDROCHLORIDE 25 mg/1 1
INACTIVE INGREDIENTS: D&C RED NO. 27 ALUMINUM LAKE; D&C RED NO. 30 ALUMINUM LAKE; DEXTROSE MONOHYDRATE; ETHYLCELLULOSE, UNSPECIFIED; FD&C BLUE NO. 1 ALUMINUM LAKE; HYDROXYPROPYL CELLULOSE, UNSPECIFIED; MAGNESIUM STEARATE; MANNITOL; STEARIC ACID; SUCRALOSE; SUCROSE

CVS 44-685-Allergy Delisted

Active ingredient (in each chewable tablet)

Diphenhydramine HCl 25 mg

Purpose

Antihistamine

Uses

- temporarily relieves these symptoms due to hay fever or other upper respiratory allergies:
  - runny nose
  - itchy, watery eyes
  - sneezing
  - itching of the nose or throat
- temporarily relieves these symptoms due to the common cold:
  - sneezing
  - runny nose

Warnings

Do not use

- to make a child sleepy
- with any other product containing diphenhydramine, even one used on skin

Ask a doctor before use if you have

- a breathing problem such as emphysema or chronic bronchitis
- glaucoma
- difficulty in urination due to enlargement of the prostate gland

Ask a doctor or pharmacist before use if you are

taking sedatives or tranquilizers.

When using this product

- marked drowsiness may occur
- alcohol, sedatives, and tranquilizers may increase drowsiness
- avoid alcoholic beverages
- use caution when driving a motor vehicle or operating machinery
- excitability may occur, especially in children

If pregnant or breast-feeding,

ask a health professional before use.

Keep out of reach of children.

In case of overdose, get medical help or contact a Poison Control Center right away.

Directions

- chew or crush tablets completely before swallowing; do not swallow tablets whole
- take every 4 to 6 hours, or as directed by a doctor
- do not take more than 6 doses in 24 hours

adults and children 12 years and over | 1 to 2 chewable tablets
children 6 to under 12 years | 1 chewable tablet
children under 6 years | do not use

Other information

- TAMPER EVIDENT: DO NOT USE IF OUTER PACKAGE IS OPENED OR BLISTER IS TORN OR BROKEN
- store at 25ºC (77ºF); excursions permitted between 15º-30ºC (59º-86ºF)
- avoid high humidity
- see end flap for expiration date and lot number

Inactive ingredients

D&C red #27 aluminum lake, D&C red #30 aluminum lake, dextrates hydrated, ethylcellulose, FD&C blue #1 aluminum lake, flavor, hydroxypropyl cellulose, magnesium stearate, mannitol, stearic acid, sucralose, sucrose

Questions or comments?

1-800-426-9391

Principal Display Panel

♥CVS Health®

Chewable Tablets

NDC 69842-685-44

Allergy Relief

DIPHENHYDRAMINE
HYDROCHLORIDE, 25 mg
CHEWABLE TABLETS
Antihistamine

Relief of:
• Sneezing
• Runny nose
• Itchy, watery eyes
• Itchy throat

For Ages 6 Years & Over

18 CHEWABLE TABLETS

Actual Size

Grape Flavored

Chew or crush
tablets completely
before swallowing.

TAMPER EVIDENT: DO NOT
USE IF PACKAGE IS OPENED
OR IF BLISTER UNIT IS
TORN, BROKEN OR SHOWS
ANY SIGNS OF TAMPERING

Distributed by: CVS Pharmacy, Inc.
One CVS Drive, Woonsocket, RI 02895
© 2024 CVS/pharmacy
CVS.com® 1-800-SHOP CVS
V-18615

50844 REV0119B68544

100% money back
guaranteed.
CVS.com/returnpolicy

CVS 44-685